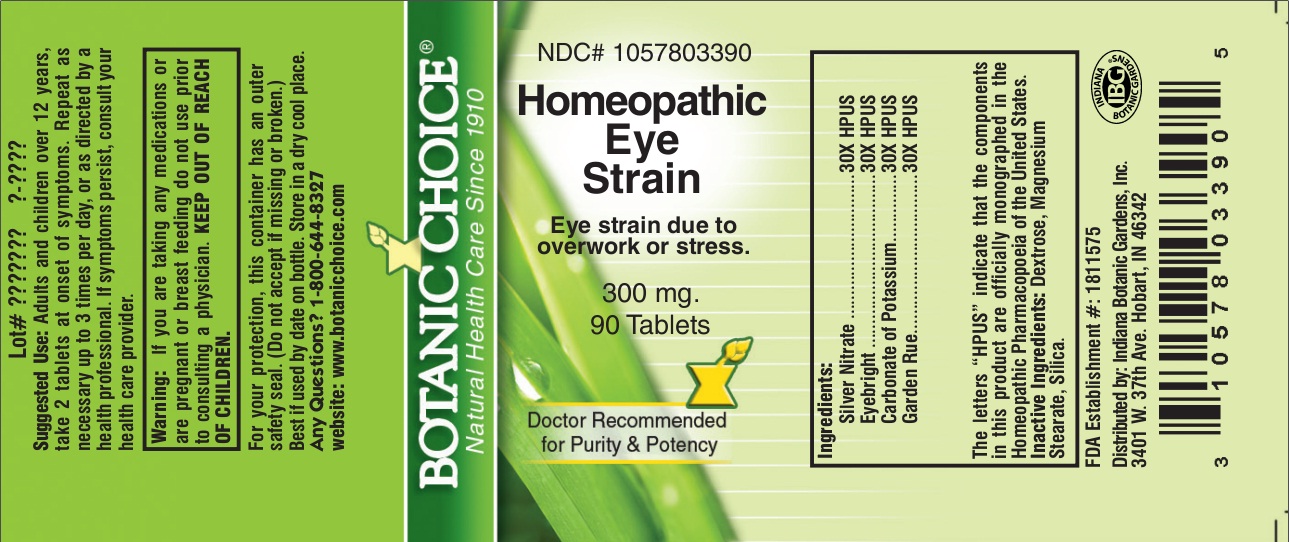 DRUG LABEL: Homeopathic Eye Strain
NDC: 10578-033 | Form: TABLET
Manufacturer: Indiana Botanic Gardens
Category: homeopathic | Type: HUMAN OTC DRUG LABEL
Date: 20131001

ACTIVE INGREDIENTS: SILVER NITRATE 30 [hp_X]/1 1; EUPHRASIA STRICTA 30 [hp_X]/1 1; POTASSIUM CARBONATE 30 [hp_X]/1 1; RUTA GRAVEOLENS FLOWERING TOP 30 [hp_X]/1 1
INACTIVE INGREDIENTS: DEXTROSE; MAGNESIUM STEARATE; SILICON DIOXIDE

Homeopathic Eye Strain

Suggested Use:

Adults and children over 12 years, take 2 tablets at onset of symptoms. Repeat as necessary up to 3 times per day, or as directed by a health professional.

STOP USE

If symptoms persist, consult your health care provider.

Warning:

If you are taking any medications or are pregnant or breast feeding do not use prior to consulting a physician.

KEEP OUT OF REACH OF CHILDREN.

For your protection, this container has an outer safety seal. (Do not accept if missing or broken.) Best if used by date on bottle. Store in a dry cool place.

Any Questions? 1-800-644-8327

website: www.botanicchoice.com

INDICATIONS AND USAGE

Eye strain due to overwork or stress.

PURPOSE

Eye strain due to overwork or stress.

Ingredients:

Silver Nitrate ..............................30X HPUS

Eyebright ....................................30X HPUS

Carbonate of Potassium ..............30X HPUS

Garden Rue .................................30X HPUS

The letters "HPUS" indicate that the components in this product are officially monographed in the Homeopathic Pharmacopoeia of the United States.

Inactive Ingredients:

Dextrose, Magnesium Stearate, Silica.

FDA Establishment #: 1811575

Distributed by: Indiana Botanic Gardens, Inc.

3401 W. 37th Ave. Hobart, IN 46342

Botanic Choice

Natural Health Care Since 1910

NDC# 1057803390

Homeopathic Eye Strain

Eye strain due to overwork or stress.

300 mg.

90 Tablets